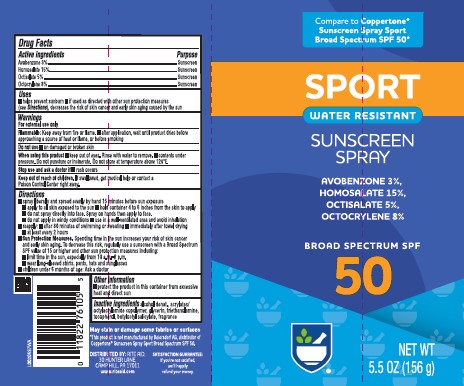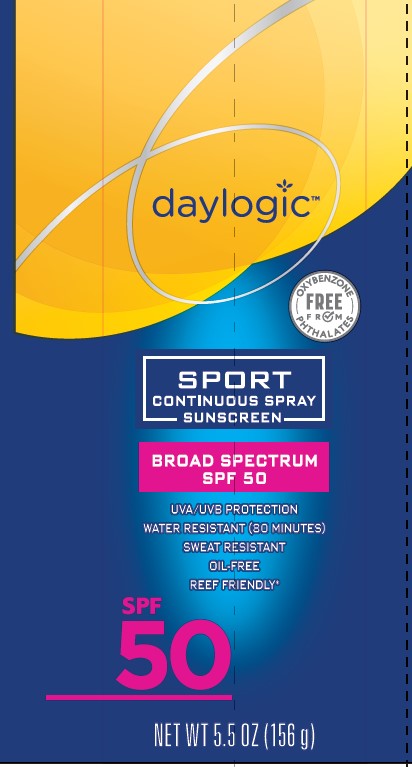 DRUG LABEL: sunscreen
NDC: 11822-0938 | Form: SPRAY
Manufacturer: Rite Aid Corporation
Category: otc | Type: HUMAN OTC DRUG LABEL
Date: 20260202

ACTIVE INGREDIENTS: AVOBENZONE 30 mg/1 g; HOMOSALATE 150 mg/1 g; OCTISALATE 50 mg/1 g; OCTOCRYLENE 80 mg/1 g
INACTIVE INGREDIENTS: ALCOHOL; ACRYLATE/ISOBUTYL METHACRYLATE/N-TERT-OCTYLACRYLAMIDE COPOLYMER (75000 MW); GLYCERIN; TROLAMINE; TOCOPHEROL; BUTYLOCTYL SALICYLATE

Rite Aid_Daylogic 938.002/938AB
Sport Sunscreen Spray SPF 50

Active Ingredients

Avobenzone 3%

Homosalate 15%

Octisalate 5%

Octocrylene 8%

Purpose

Sunscreen

Uses

■ helps prevent sunburn

■ if used as directed with other sun protection measures (see Directions), decreases the risk of skin cancer and early skin aging caused by the sun

Warnings

For external use only

Flammable

Keep away from fire or flame.

- after application, wait until product dries before approaching a source of heat or flame, or before smoking

Do not use

- on damaged or broken skin

When using this product

- keep out of eyes. Rinse with water to remove.
- contents under pressure. Do not puncture or incinerate. Do not store at temperature above 120ºF.

stop use and ask a doctor if

- rash occurs

keep out of reach of children

if swallowed, get medical help or contact a Poison Conrol Center right away

direction

■ spray liberally and spread evenly by hand 15 minutes before sun exposure
■ apply to all skin exposed to the sun
■ hold container 4 to 6 inches from the skin to apply
■ do not spray directly into face. Spray on hands then apply to face.
■ do not apply in windy conditions
■ use in a well-ventilated area and avoid inhalation
■ reapply:
■ after 80 minutes of swimming or sweating
■ immediately after towel drying
■ at least every 2 hours
■ Sun Protection Measures. Spending time in the sun increases your risk of skin cancer and early skin aging. To decrease this risk, regularly use a sunscreen with a Broad Spectrum SPF value of 15 or higher and other sun protection measures including:
■ limit time in the sun, especially from 10 a.m.–2 p.m.
■ wear long-sleeved shirts, pants, hats and sunglasses
■ children under 6 months of age: Ask a doctor

other information

- protect the product in the container from excessive heat and direct sun

Inactive ingredients

alcohol denat., acrylates/octylacrylamide copolymer, glycerin, triethanolamine, tocopherol, butyloctyl salicylate, fragrance

ADVERSE REACTION

May stain or damage some fabrics of surfaces

*This product is not manufactured by Beiensdorf AG, distributer of Coppertone®Sunscreen Spray Broad Spectrum SPF 50.

DISTRIBUTED BY: RITE AID

30 HUNTER LANE

CAMP HILL, PA 17011

www.riteaid.com

Satisfation Guarantee

If you're not satisfied, we'll happily refund your money.

principal display panel

daylogic

FREE FROM OXYBENZONE - PHTHALATES

SPORT

CONTINUOUS SPRAY SUNSCREEN

BROAD SPECTRU,M SPF 50

UVA/UVB PROTECTION

WATER RESISTANT (80 MINUTES)

SWEAT RESISTANT

OIL-FREE

REEF FRIENDLY*

SPF 50

NET WT 5.5 OZ (156 g)

principal display panel

Compare to Coppertone®Sunscreen Spray Sport Broad Spectrum SPF 50*

SPORT

WATER RESISTANT

SUNSCREEN SPRAY

Avobenzone 3%

Homosalate 15%

Octisalate 5%

Octocrylene 8%

BROAD SPECTRUM SPF 50

NET WT 5.5 OZ (156 g)